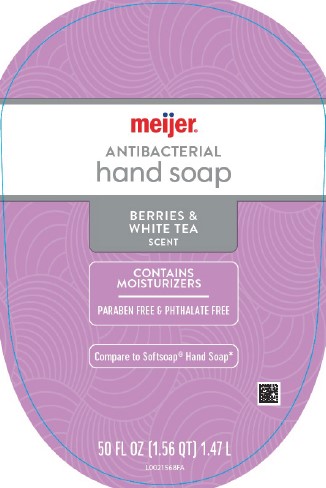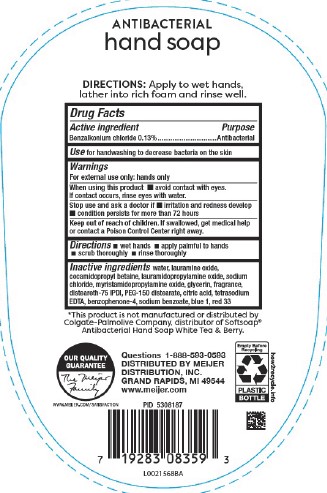 DRUG LABEL: Antibacterial
NDC: 41250-976 | Form: SOAP
Manufacturer: Meijer, Inc.
Category: otc | Type: HUMAN OTC DRUG LABEL
Date: 20260220

ACTIVE INGREDIENTS: BENZALKONIUM CHLORIDE 1.3 mg/1 mL
INACTIVE INGREDIENTS: WATER; LAURAMINE OXIDE; COCAMIDOPROPYL BETAINE; LAURAMIDOPROPYLAMINE OXIDE; SODIUM CHLORIDE; MYRISTAMIDOPROPYLAMINE OXIDE; GLYCERIN; DISTEARETH-75 ISOPHORONE DIISOCYANATE; PEG-150 DISTEARATE; CITRIC ACID MONOHYDRATE; EDETATE SODIUM; SULISOBENZONE; SODIUM BENZOATE; FD&C BLUE NO. 1; D&C RED NO. 33

Meijer 897.003/897AC
Antibacterial Hand Soap Berries & White Tea

Claims

ANTIBACTERIAL

hand saop

DIRECTIONS:

Apply to wet hands, lather into rich foam and rinse well.

Active Ingredient

Benzalkonium chloride 0.13%

Purpose

Antibacterial

Use

for handwashing to decrease bacteria on the skin

Warnings

For external use only: hands only

When using this product

- avoid contact with eyes. If contact occurs, rinse eyes with water.

stop use and ask a doctor if

- if irritation and redness develop
- comdition persists for more than 72 hours

Keep out of reach of children.

If swallowed, get medical help or contact a Poison Control Center right away.

Directions

- wet hands
- apply palmful to hands
- scrub thoroughly
- rinse thoroughly

Inactive ingredients

water, lauramine oxide, cocamidopropyl betaine, lauramidopropylamine oxide, sodium chloride, myristamidopropylamine oxide, glycerin, fragrance, disteareth-75 IPDI, PEG-150 distearate, citric acid, tetrasodium EDTA, benzophenone-4, sodium benzoate, blue 1, red 33

Disclaimer

*This product is not manufactured or distribute by the Colgate-Palmolive Company, distributor of SoftsoapAntibacterial Hand Soap White Tea & Berry.

Adverse reaction

Questions 1-888-593-0593

DISTRIBUTED BY

MEIJER DISTRIBUTION, INC

GRAND RAPIDS, MI 49544

www.meijer.com

OUR QUALITY GUARANTEE

The Meijer Family

WWW.MEIJER.COM/SATISFACTION

Empty Before Recycling

PLASTIC BOTTLE

how2recycle.info

Principal Panel Display

meijer®

ANTIBACTERIAL

hand soap

BERRIES & WHITE TEA SCENT

CONTAINS MOISTURIZERS

PARABEN FREE & PHTHALATE FREE

Compare to Softsoap®Hand Soap*

50 FL OZ (1.56 QT) 1.47 L